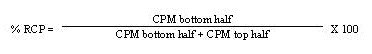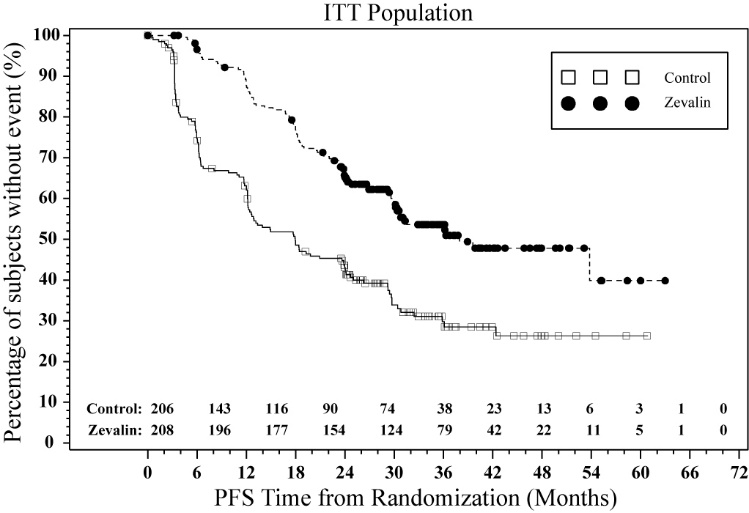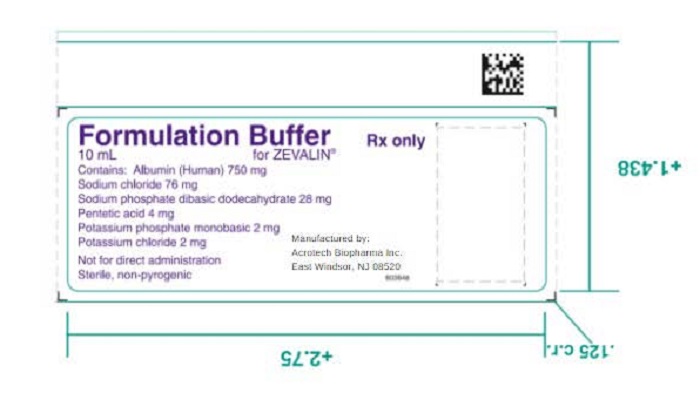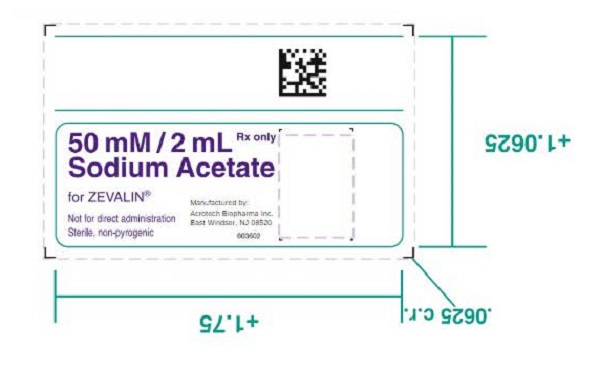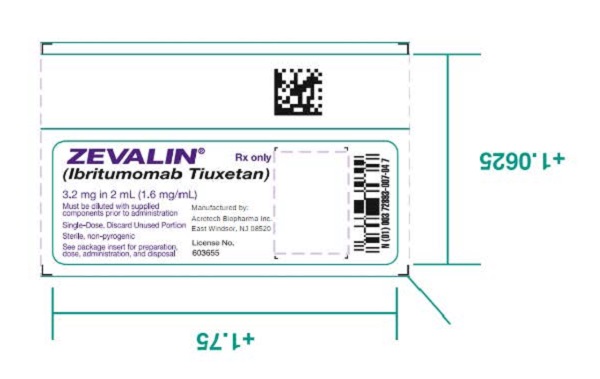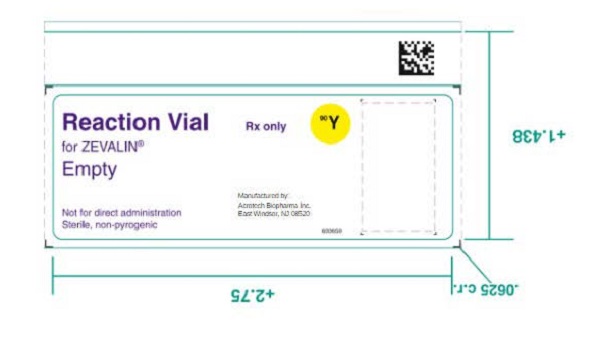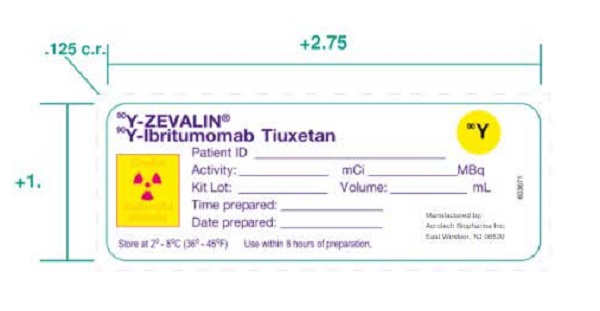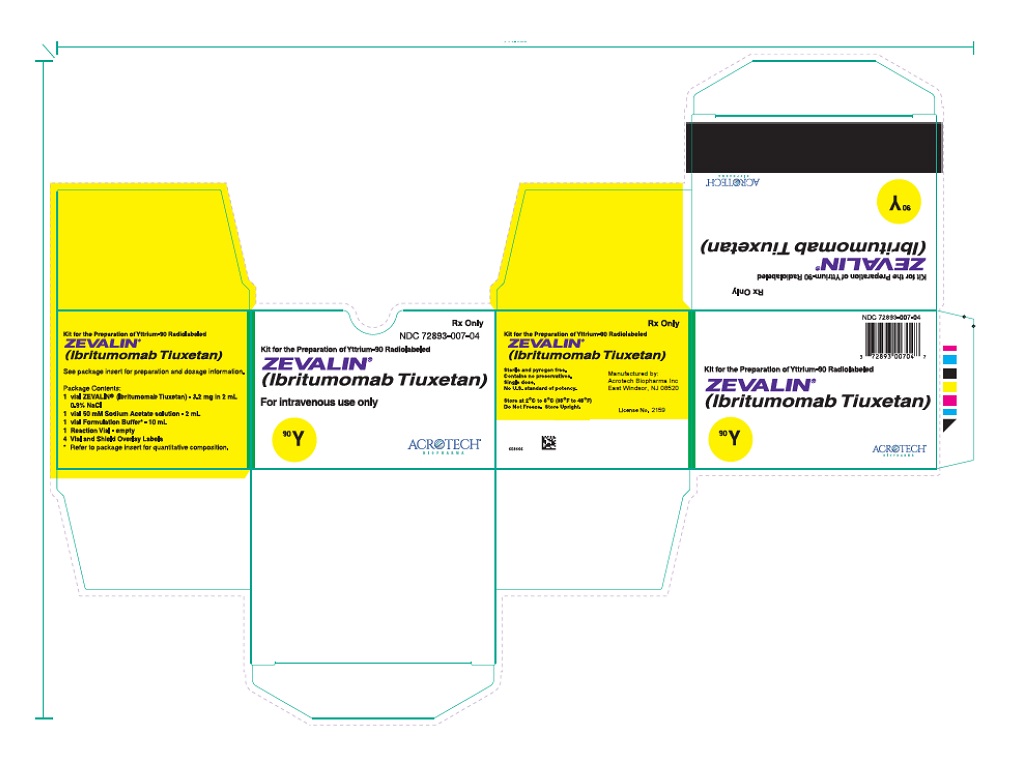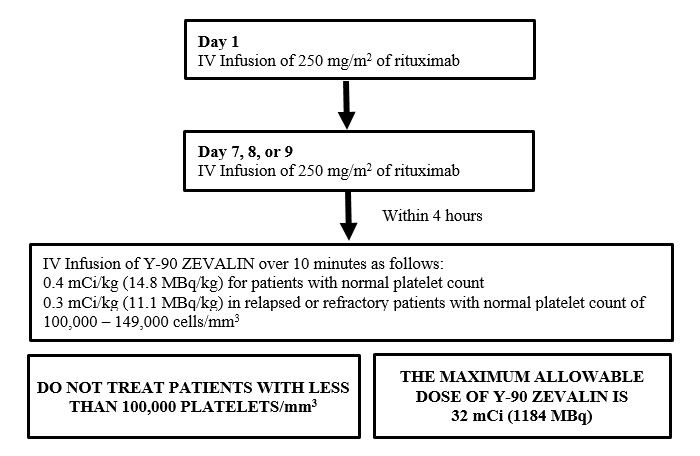 DRUG LABEL: Zevalin
NDC: 72893-007 | Form: KIT | Route: INTRAVENOUS
Manufacturer: Acrotech Biopharma Inc
Category: prescription | Type: Human Prescription Drug Label
Date: 20230425

ACTIVE INGREDIENTS: IBRITUMOMAB TIUXETAN 1.6 mg/1 mL
INACTIVE INGREDIENTS: SODIUM CHLORIDE 8.8 mg/1 mL; WATER; ALBUMIN HUMAN 75 mg/1 mL; SODIUM CHLORIDE 7.6 mg/1 mL; SODIUM PHOSPHATE, DIBASIC, DODECAHYDRATE 2.8 mg/1 mL; PENTETIC ACID 0.4 mg/1 mL; POTASSIUM PHOSPHATE, MONOBASIC 0.2 mg/1 mL; SODIUM HYDROXIDE 0.2 mg/1 mL; HYDROCHLORIC ACID; WATER; SODIUM ACETATE 6.8 mg/1 mL; WATER

HIGHLIGHTS OF PRESCRIBING INFORMATION

These highlights do not include all the information needed to use ZEVALIN safely and effectively. See full prescribing information for ZEVALIN.
ZEVALIN® (ibritumomab tiuxetan) injection, for intravenous use
Initial U.S. Approval: 2002

WARNING: SERIOUS INFUSION REACTIONS, PROLONGED AND SEVERE CYTOPENIAS, and SEVERE CUTANEOUS AND MUCOCUTANEOUS REACTIONS

See full prescribing information for complete boxed warning

- Serious Infusion Reactions, some fatal, may occur within 24 hours of rituximab infusion. (5.1)
- Prolonged and Severe Cytopenias occur in most patients. (5.2)
- Severe Cutaneous and Mucocutaneous Reactions, some fatal, reported with Zevalin therapeutic regimen. (5.3, 6.2)
- Do not exceed 32 mCi (1184 MBq) of Y-90 Zevalin. (2.2)

1 INDICATIONS AND USAGE

Zevalin is a CD20-directed radiotherapeutic antibody administered as part of the Zevalin therapeutic regimen indicated for the treatment of adult patients with:

- relapsed or refractory, low-grade or follicular B-cell non-Hodgkin's lymphoma (NHL) (1.1).
- previously untreated follicular NHL who achieve a partial or complete response to first-line chemotherapy (1.2).

2 DOSAGE AND ADMINISTRATION

- Day 1: Administer rituximab 250 mg/m^2 intravenous infusion. (2.2)
- Day 7, 8, or 9:
- Administer rituximab 250 mg/m^2 intravenous infusion. (2.2)
- If platelets at least 150,000/mm^3: Within 4 hours after rituximab infusion, administer 0.4 mCi/kg (14.8 MBq per kg) Y-90 Zevalin intravenous infusion.
- If platelets 100,000 to 149,000/mm^3 in relapsed or refractory patients: Within 4 hours after rituximab infusion, administer 0.3 mCi/kg (11.1 MBq per kg) Y-90 Zevalin intravenous infusion.

3 DOSAGE FORMS AND STRENGTHS

- Injection: 3.2 mg per 2 mL in a single-dose vial. (3)

4 CONTRAINDICATIONS

None.

5 WARNINGS AND PRECAUTIONS

- Serious Infusion Reactions: Immediately discontinue rituximab and Y-90 Zevalin. (5.1, 6.1)
- Prolonged and Severe Cytopenias: Do not administer Zevalin to patients with ≥ 25% lymphoma marrow involvement or impaired bone marrow reserve. (5.2, 6.1)
- Severe Cutaneous and Mucocutaneous Reactions: Discontinue rituximab and Zevalin infusions if patients develop severe cutaneous or mucocutaneous reactions. (5.3, 6.2)
- Development of Leukemia and Myelodysplastic Syndrome: Monitor patients for hematological toxicity including secondary malignancies. (5.4, 6.1)
- Extravasation: Monitor for extravasation and terminate infusion if it occurs. Resume infusion in another limb. (5.5, 6.2)
- Immunization: Do not administer live viral vaccines to patients who recently received Zevalin. (5.6)
- Embryo-fetal Toxicity: May cause fetal harm. Advise patients of potential risk to a fetus and to use effective contraception. (5.8, 8.1, 8.3)

6 ADVERSE REACTIONS

Common adverse reactions (> 10%) in clinical trials were: cytopenias, fatigue, nasopharyngitis, nausea, abdominal pain, asthenia, cough, diarrhea, and pyrexia. (6)

To report SUSPECTED ADVERSE REACTIONS, contact Acrotech Biopharma Inc. at 1-866-298-8433 or FDA at 1-800-FDA-1088 or www.fda.gov/medwatch

7 DRUG INTERACTIONS

- Monitor patients receiving medications that interfere with platelet function or coagulation more frequently for thrombocytopenia. (7)

8 USE IN SPECIFIC POPULATIONS

- Lactation: Advise women not to breastfeed. (8.2)

FULL PRESCRIBING INFORMATION

WARNING: SERIOUS INFUSION REACTIONS, PROLONGED AND SEVERE CYTOPENIAS, and SEVERE CUTANEOUS AND MUCOCUTANEOUS REACTIONS

Serious Infusion Reactions: Deaths have occurred within 24 hours of rituximab infusion, an essential component of the Zevalin therapeutic regimen. These fatalities were associated with hypoxia, pulmonary infiltrates, acute respiratory distress syndrome, myocardial infarction, ventricular fibrillation, or cardiogenic shock. Most (80%) fatalities occurred with the first rituximab infusion [see Warnings and Precautions (5.1) and Adverse Reactions (6.1)]. Discontinue rituximab and Y-90 Zevalin infusions in patients who develop severe infusion reactions.
Prolonged and Severe Cytopenias: Y-90 Zevalin administration results in severe and prolonged cytopenias in most patients. Do not administer Y-90 Zevalin to patients with ≥ 25% lymphoma marrow involvement and/or impaired bone marrow reserve [see Warnings and Precautions (5.2) and Adverse Reactions (6.1)].
Severe Cutaneous and Mucocutaneous Reactions: Severe cutaneous and mucocutaneous reactions, some fatal, can occur with the Zevalin therapeutic regimen. Discontinue rituximab and Y-90 Zevalin infusions in patients experiencing severe cutaneous or mucocutaneous reactions [see Warnings and Precautions (5.3) and Adverse Reactions (6.2)].
Dosing: The dose of Y-90 Zevalin should not exceed 32 mCi (1184 MBq) [see Dosage and Administration (2.2)].

1 INDICATIONS AND USAGE

1.1 Relapsed or Refractory, Low-grade or Follicular NHL

Zevalin is indicated for the treatment of adult patients with relapsed or refractory, low-grade or follicular B-cell non-Hodgkin's lymphoma (NHL).

1.2 Previously Untreated Follicular NHL

Zevalin is indicated for the treatment of previously untreated follicular NHL in adult patients who achieve a partial or complete response to first-line chemotherapy.

2 DOSAGE AND ADMINISTRATION

2.1 Recommended Dosing Schedule

- Administer the Zevalin therapeutic regimen as outlined below.
- Initiate the Zevalin therapeutic regimen following recovery of platelet counts to 150,000/mm^3 or more at least 6 weeks, but no more than 12 weeks, following the last dose of first-line chemotherapy.
- Only administer rituximab/Zevalin in facilities where immediate access to resuscitative measures is available.

Overview of Dosing Schedule

2.2 Zevalin Therapeutic Regimen Dosage and Administration

Day 1:

- Premedicate with acetaminophen 650 mg orally and diphenhydramine 50 mg orally prior to rituximab infusion.
- Administer rituximab 250 mg/m^2 intravenously at an initial rate of 50 mg/hr. In the absence of infusion reactions, escalate the infusion rate in 50 mg/hr increments every 30 minutes to a maximum of 400 mg/hr. Do not mix or dilute rituximab with other drugs.
- Immediately stop the rituximab infusion for serious infusion reactions and discontinue the Zevalin therapeutic regimen [see Boxed Warning and Warnings and Precautions (5.1)].
- Temporarily slow or interrupt the rituximab infusion for less severe infusion reactions. If symptoms improve, continue the infusion at one-half the previous rate.

Day 7, 8 or 9:

- Premedicate with acetaminophen 650 mg orally and diphenhydramine 50 mg orally prior to rituximab infusion.
- Administer rituximab 250 mg/m^2 intravenously at an initial rate of 100 mg/hr. Increase rate by 100 mg/hr increments at 30 minute intervals, to a maximum of 400 mg/hr, as tolerated. If infusion reactions occurred during rituximab infusion on Day 1 of treatment, administer rituximab at an initial rate of 50 mg/hr and escalate the infusion rate in 50 mg/hr increments every 30 minutes to a maximum of 400 mg/hr.
- Administer Y-90 Zevalin injection through a free flowing intravenous line within 4 hours following completion of rituximab infusion. Use a 0.22 micron low-protein-binding in-line filter between the syringe and the infusion port. After infusion, flush the line with at least 10 mL of normal saline.
  - If platelet count at least 150,000/mm^3, administer Y-90 Zevalin over 10 minutes as an intravenous infusion at a dose of Y-90 0.4 mCi per kg (14.8 MBq per kg) actual body weight.
  - If platelet count 100,000 to 149,000/mm^3, in relapsed or refractory patients, administer Y-90 Zevalin over 10 minutes as an intravenous infusion at a dose of Y-90 0.3 mCi per kg (11.1 MBq per kg) actual body weight.
  - Do not administer more than 32 mCi (1184 MBq) Y-90 Zevalin dose regardless of the patient’s body weight.
- Monitor patients closely for evidence of extravasation during the infusion of Y-90 Zevalin. Immediately stop infusion and restart in another limb if any signs or symptoms of extravasation occur [see Warnings and Precautions (5.5)].

2.3 Directions for Preparation of Radiolabeled Y-90 Zevalin Doses

A clearly-labeled kit is required for preparation of Yttrium-90 (Y-90) Zevalin. Follow the detailed instructions for the preparation of radiolabeled Zevalin [see Dosage and Administration (2.4)].

Required materials not supplied in the kit:

1. Yttrium-90 Chloride Sterile Solution
2. Three sterile 1 mL plastic syringes
3. One sterile 3 mL plastic syringe
4. Two sterile 10 mL plastic syringes with 18-20 G needles
5. ITLC silica gel strips
6. 0.9% Sodium Chloride aqueous solution for the chromatography solvent
7. Developing chamber for chromatography
8. Suitable radioactivity counting apparatus
9. Filter, 0.22 micrometer, low-protein-binding
10. Appropriate acrylic shielding for reaction vial and syringe for Y-90

Method:

1. Allow contents of the refrigerated Y-90 Zevalin kit (Zevalin vial, 50 mM sodium acetate vial, and formulation buffer vial) to reach room temperature.
2. Place the empty reaction vial in an appropriate acrylic shield.
3. Determine the amount of each component needed:
  1. Calculate volume of Y-90 Chloride equivalent to 40 mCi based on the activity concentration of the Y-90 Chloride stock.
  2. The volume of 50 mM Sodium Acetate solution needed is 1.2 times the volume of Y-90 Chloride solution determined in step 3.a, above.
  3. Calculate the volume of formulation buffer needed to bring the reaction vial contents to a final volume of 10 mL.
4. Transfer the calculated volume of 50 mM Sodium Acetate to the empty reaction vial. Coat the entire inner surface of the reaction vial by gentle inversion or rolling.
5. Transfer 40 mCi of Y-90 Chloride to the reaction vial using an acrylic shielded syringe. Mix the two solutions by gentle inversion or rolling.
6. Transfer 1.3 mL of Zevalin (ibritumomab tiuxetan) to the reaction vial. Do not shake or agitate the vial contents.
7. Allow the labeling reaction to proceed at room temperature for 5 minutes. A shorter or longer reaction time may adversely alter the final labeled product.
8. Immediately after the 5-minute incubation period, transfer the calculated volume of formulation buffer from step 3.c. to the reaction vial. Gently add the formulation buffer down the side of the reaction vial. If necessary, withdraw an equal volume of air to normalize pressure.
9. Measure the final product for total activity using a radioactivity calibration system suitable for the measurement of Y-90.
10. Using the supplied labels, record the date and time of preparation, the total activity and volume, and the date and time of expiration, and affix these labels to the shielded reaction vial container.
11. Patient Dose: Calculate the volume required for a Y-90 Zevalin dose [see Dosage and Administration (2.2)]. Withdraw the required volume from the reaction vial. Assay the syringe in the dose calibrator suitable for the measurement of Y-90. The measured dose must be within 10% of the prescribed dose of Y-90 Zevalin and must not exceed 32 mCi (1184 MBq). Using the supplied labels, record the patient identifier, total activity and volume and the date and time of expiration, and affix these labels to the syringe and shielded unit dose container.
12. Determine Radiochemical Purity [see Dosage and Administration (2.4)].
13. Store Yttrium-90 Zevalin at 2-8°C (36-46°F) until use and administer within 8 hours of radiolabeling. Immediately prior to administration, assay the syringe and contents using a radioactivity calibration system suitable for the measurement of Y-90.

2.4 Procedure for Determining Radiochemical Purity

Use the following procedures for radiolabeling Y-90 Zevalin:

1. Place a small drop of Y-90 Zevalin at the origin of an ITLC silica gel strip.
2. Place the ITLC silica gel strip into a chromatography chamber with the origin at the bottom and the solvent front at the top. Allow the solvent (0.9% NaCl) to migrate at least 5 cm from the bottom of the strip. Remove the strip from the chamber and cut the strip in half. Count each half of the ITLC silica gel strip for one minute (CPM) with a suitable counting apparatus.
3. Calculate the percent RCP as follows:
4. Repeat the ITLC procedure if the radiochemical purity is <95%. If repeat testing confirms that radiochemical purity is <95%, do not administer the Y-90 Zevalin dose.

2.5 Radiation Dosimetry

During clinical trials with Zevalin, estimations of radiation-absorbed doses for Y-90 Zevalin were performed using sequential whole body images and the MIRDOSE 3 software program. The estimated radiation absorbed doses to organs and marrow from a course of the Zevalin therapeutic regimen are summarized in Table 1. Absorbed dose estimates for the lower large intestine, upper large intestine, and small intestine have been modified from the standard MIRDOSE 3 output to account for the assumption that activity is within the intestine wall rather than the intestine contents.

Table 1 . Estimated Radiation Absorbed Doses from Y-90 Zevalin
Organ | Y-90 Zevalin cGy /mCi (mGy/MBq)
Organ | Median | Range
Spleen [Organ region of interest] | 34.78 (9.4) | 6.66 - 74.00 (1.8 - 20.0)
Liver | 17.76 (4.8) | 10.73 - 29.97 (2.9 - 8.1)
Lower Large Intestinal Wall | 17.39 (4.7) | 11.47 - 30.34 (3.1 - 8.2)
Upper Large Intestinal Wall | 13.32 (3.6) | 7.40 - 24.79 (2.0 - 6.7)
Heart Wall | 10.73 (2.9) | 5.55 - 11.84 (1.5 - 3.2)
Lungs | 7.4 (2) | 4.44 - 12.58 (1.2 -3.4)
Testes | 5.55 (1.5) | 3.70 - 15.91 (1.0 - 4.3)
Small Intestine | 5.18 (1.4) | 2.96 - 7.77 (0.8 - 2.1)
Red Marrow [Sacrum region of interest] | 4.81 (1.3) | 2.22 - 6.66 (0.6 - 1.8)
Urinary Bladder Wall [Whole body region of interest] | 3.33 (0.9) | 2.59 - 4.81 (0.7 - 1.3)
Bone Surfaces | 3.33 (0.9) | 1.85 - 4.44 (0.5 - 1.2)
Total Body | 1.85 (0.5) | 1.48 - 2.59 (0.4 - 0.7)
Ovaries | 1.48 (0.4) | 1.11 - 1.85 (0.3 - 0.5)
Uterus | 1.48 (0.4) | 1.11 - 1.85 (0.3 - 0.5)
Adrenals | 1.11 (0.3) | 0.74 - 1.85 (0.2 - 0.5)
Brain | 1.11 (0.3) | 0.74 - 1.85 (0.2 - 0.5)
Breasts | 1.11 (0.3) | 0.74 - 1.85 (0.2 - 0.5)
Gallbladder Wall | 1.11 (0.3) | 0.74 - 1.85 (0.2 - 0.5)
Muscle | 1.11 (0.3) | 0.74 - 1.85 (0.2 - 0.5)
Pancreas | 1.11 (0.3) | 0.74 - 1.85 (0.2 - 0.5)
Skin | 1.11 (0.3) | 0.74 - 1.85 (0.2 - 0.5)
Stomach | 1.11 (0.3) | 0.74 - 1.85 (0.2 - 0.5)
Thymus | 1.11 (0.3) | 0.74 - 1.85 (0.2 - 0.5)
Thyroid | 1.11 (0.3) | 0.74 - 1.85 (0.2 - 0.5)
Kidneys | 0.37 (0.1) | 0.00 - 1.11 (0.0 - 0.3)

3 DOSAGE FORMS AND STRENGTHS

Injection: 3.2 mg ibritumomab tiuxetan per 2 mL as a clear, colorless solution, that may contain translucent particles, in a single-dose vial.

4 CONTRAINDICATIONS

None.

5 WARNINGS AND PRECAUTIONS

5.1 Serious Infusion Reactions

Rituximab, alone or as a component of the Zevalin therapeutic regimen, can cause severe, including fatal, infusion reactions. These reactions typically occur during the first rituximab infusion with time to onset of 30 to 120 minutes. Signs and symptoms of severe infusion reactions may include urticaria, hypotension, angioedema, hypoxia, bronchospasm, pulmonary infiltrates, acute respiratory distress syndrome, myocardial infarction, ventricular fibrillation, and cardiogenic shock. Temporarily slow or interrupt the rituximab infusion for less severe infusion reactions. Immediately discontinue rituximab and Y-90 Zevalin administration for severe infusion reactions. Only administer rituximab/Zevalin in facilities where immediate access to resuscitative measures is available [see Boxed Warning and Dosage and Administration (2.2)]. See also prescribing information for rituximab.

5.2 Prolonged and Severe Cytopenias

Cytopenias with delayed onset and prolonged duration, some complicated by hemorrhage and severe infection, are the most common severe adverse reactions of the Zevalin therapeutic regimen. When used according to recommended doses, the incidences of severe thrombocytopenia and neutropenia are greater in patients with mild baseline thrombocytopenia (≥ 100,000 but ≤ 149,000/mm^3) compared to those with normal pretreatment platelet counts. Severe cytopenias persisting more than 12 weeks following administration can occur. Monitor complete blood counts (CBC) and platelet counts following the Zevalin therapeutic regimen weekly until levels recover or as clinically indicated [see Boxed Warning and Adverse Reactions (6.1)].

Do not administer the Zevalin therapeutic regimen to patients with ≥ 25% lymphoma marrow involvement and/or impaired bone marrow reserve. Monitor patients for cytopenias and their complications (e.g., febrile neutropenia, hemorrhage) for up to 3 months after use of the Zevalin therapeutic regimen. Avoid using drugs which interfere with platelet function or coagulation following the Zevalin therapeutic regimen.

5.3 Severe Cutaneous and Mucocutaneous Reactions

Erythema multiforme, Stevens-Johnson syndrome, toxic epidermal necrolysis, bullous dermatitis, and exfoliative dermatitis, some fatal, were reported in post-marketing experience. The time to onset of these reactions was variable, ranging from a few days to 4 months after administration of the Zevalin therapeutic regimen. Discontinue the Zevalin therapeutic regimen in patients experiencing a severe cutaneous or mucocutaneous reaction [see Boxed Warning and Adverse Reactions (6.2)].

5.4 Risk of Developing Myelodysplastic Syndrome, Leukemia, and Other Malignancies

The radiation dose resulting from therapeutic exposure to Y-90 radiolabeled Zevalin may result in secondary malignancies.

Myelodysplastic syndrome (MDS) and/or acute myelogenous leukemia (AML) were reported in 5.2% (11/211) of patients with relapsed or refractory NHL enrolled in clinical studies and 1.5% (8/535) of patients included in the expanded-access trial, with median follow-up of 6.5 and 4.4 years, respectively. Among the 19 reported cases, the median time to the diagnosis of MDS or AML was 1.9 years following treatment with the Zevalin therapeutic regimen; however, the cumulative incidence continues to increase [see Adverse Reactions (6.1)].

Among 204 patients receiving Y-90 Zevalin following first-line chemotherapy, 26 (12.7%) patients in the Zevalin arm developed a second primary malignancy compared to 14 (6.8%) of patients in the control arm. Seven patients (3.4%, 7/204) were diagnosed with MDS/AML after receiving Zevalin, compared to one patient (0.5%, 1/205) in the control arm, with a median follow-up of 7.3 years. Deaths due to second primary malignancy included 8 (3.9%) patients in the Zevalin arm compared to 3 (1.5%) patients in the control arm. Deaths due to MDS/AML included five (2.5%) patients in the Zevalin arm compared to no patients in the control arm.

Monitor patients for hematological toxicity including development of MDS or AML.

5.5 Extravasation

Monitor patients closely for evidence of extravasation during Zevalin infusion. Immediately terminate the infusion if signs or symptoms of extravasation occur and restart in another limb [see Dosage and Administration (2.2)] .

5.6 Risks of Immunization

The safety of immunization with live viral vaccines following the Zevalin therapeutic regimen has not been studied. Do not administer live viral vaccines to patients who have recently received Zevalin. The ability to generate an immune response to any vaccine following the Zevalin therapeutic regimen has not been studied.

5.7 Radionuclide Precautions

During and after radiolabeling Zevalin with Y-90, minimize radiation exposure to patients and to medical personnel, consistent with institutional good radiation safety practices and patient management procedures.

5.8 Embryo-Fetal Toxicity

Based on its radioactivity, Y-90 Zevalin may cause fetal harm when administered to a pregnant woman. Advise pregnant women of the potential risk to a fetus. Advise females of reproductive potential and males with female partners of reproductive potential to use effective contraception during treatment and for a minimum of twelve months after the last dose [see Use in Specific Populations (8.1, 8.3) and Clinical Pharmacology (12.1)] .

6 ADVERSE REACTIONS

The following serious adverse reactions are discussed in greater detail in other sections of the label:

- Serious Infusion Reactions [see Boxed Warning andWarnings and Precautions (5.1)] .
- Prolonged and Severe Cytopenias [see Boxed Warning and Warnings and Precautions (5.2)].
- Severe Cutaneous and Mucocutaneous Reactions [see Boxed Warning and Warnings and Precautions (5.3)].
- Leukemia and Myelodysplastic Syndrome [see Warnings and Precautions (5.4)].

6.1 Clinical Trials Experience

Because clinical trials are conducted under widely varying conditions, adverse reaction rates observed in the clinical trials of a drug cannot be directly compared to rates in the clinical trials of another drug and may not reflect the rates observed in practice.

The reported safety data reflects exposure to Zevalin in 349 patients with relapsed or refractory, low-grade, follicular or transformed NHL across 5 trials (4 single arm and 1 randomized) and in 206 patients with previously untreated follicular NHL in a randomized trial (FIT study) who received any portion of the Zevalin therapeutic regimen. The safety data reflect exposure to Zevalin in 270 patients with relapsed or refractory NHL with platelet counts ≥150,000/ mm^3 who received 0.4 mCi/kg (14.8 MBq/kg) of Y-90 Zevalin (Group 1 in Table 4), 65 patients with relapsed or refractory NHL with platelet counts of ≥ 100,000 but ≤ 149,000 /mm^3 who received 0.3 mCi/kg (11.1 MBq/kg) of Y-90 Zevalin (Group 2 in Table 4), and 204 patients with previously untreated NHL with platelet counts ≥150,000/ mm^3 who received 0.4 mCi/kg (14.8 MBq/kg) of Y-90 Zevalin; all patients received a single course of Zevalin.

The most common adverse reactions of Zevalin are cytopenias, fatigue, nasopharyngitis, nausea, abdominal pain, asthenia, cough, diarrhea, and pyrexia.

The most serious adverse reactions of Zevalin are prolonged and severe cytopenias (thrombocytopenia, anemia, lymphopenia, neutropenia) and secondary malignancies.

Because the Zevalin therapeutic regimen includes the use of rituximab, see prescribing information for rituximab.

Table 2 displays selected adverse reaction incidence rates in patients who received any portion of the Zevalin therapeutic regimen (n=206) or no further therapy (n=203) following first-line chemotherapy (FIT study).

Table 2. Per-Patient Incidence (%) of Selected [Between-group difference of ≥5%] Adverse Reactions Occurring in ≥ 5% of Patients with Previously Untreated Follicular NHL Treated with the Zevalin Therapeutic Regimen
 | Zevalin (n=206) |  | Observation (n=203)
 | All Grades [NCI CTCAE version 2.0] | Grade 3-4 | All Grades |  | Grade 3-4
 | % | % | % |  | %
Gastrointestinal Disorders
Abdominal pain | 17 | 2 | 13 |  | <1
Diarrhea | 11 | 0 | 3 |  | 0
Nausea | 18 | 0 | 2 |  | 0
Body as a Whole
Asthenia | 15 | 1 | 8 |  | <1
Fatigue | 33 | 1 | 9 |  | 0
Influenza-like illness | 8 | 0 | 3 |  | 0
Pyrexia | 10 | 3 | 4 |  | 0
Musculoskeletal
Myalgia | 9 | 0 | 3 |  | 0
Metabolism
Anorexia | 8 | 0 | 2 |  | 0
Respiratory, Thoracic & Media
Cough | 11 | <1 | 5 |  | 0
Pharyngolaryngeal pain | 7 | 0 | 2 |  | 0
Epistaxis | 5 | 2 | <1 |  | 0
Nervous System
Dizziness | 7 | 0 | 2 |  | 0
Vascular
Hypertension | 7 | 3 | 2 |  | <1
Skin & Subcutaneous
Night sweats | 8 | 0 | 2 |  | 0
Petechiae | 8 | 2 | 0 |  | 0
Pruritus | 7 | 0 | 1 |  | 0
Rash | 7 | 0 | <1 |  | 0
Infections & Infestations
Bronchitis | 8 | 0 | 3 |  | 0
Nasopharyngitis | 19 | 0 | 10 |  | 0
Rhinitis | 8 | 0 | 2 |  | 0
Sinusitis | 7 | <1 | <1 |  | 0
Urinary tract infection | 7 | <1 | 3 |  | 0
Blood and Lymphatic System
Thrombocytopenia | 62 | 51 | 1 |  | 0
Neutropenia | 45 | 41 | 3 |  | 2
Anemia | 22 | 5 | 4 |  | 0
Leukopenia | 43 | 36 | 4 |  | 1
Lymphopenia | 26 | 18 | 9 |  | 5

Table 3 shows hematologic toxicities in 349 Zevalin-treated patients with relapsed or refractory, low-grade, follicular or transformed B-cell NHL. Grade 2-4 hematologic toxicity occurred in 86% of Zevalin-treated patients.

Table 3. Per-Patient Incidence (%) of Hematologic Adverse Reactions in Patients with Relapsed or Refractory Low-grade, Follicular or Transformed B-cell NHL [Occurring within the 12 weeks following the first rituximab infusion of the Zevalin therapeutic regimen] (N = 349)
 | All Grades % | Grade 3-4 %
Thrombocytopenia | 95 | 63
Neutropenia | 77 | 60
Anemia | 61 | 17
Ecchymosis | 7 | <1

Prolonged and Severe Cytopenias

Patients in clinical studies were not permitted to receive hematopoietic growth factors beginning 2 weeks prior to administration of the Zevalin therapeutic regimen.

The incidence and duration of severe hematologic toxicity in previously treated NHL patients (N=335) and in previously untreated patients (FIT study) receiving Y-90 Zevalin are shown in Table 4.

Table 4. Severe Hematologic Toxicity in Patients Receiving Zevalin
Baseline Platelet Count | Group 1 (n=270) ≥ 150,000/mm^3 | Group 2 (n=65) ≥ 100,000 but ≤ 149,000/mm^3 | FIT study (n=204) ≥ 150,000/mm^3
Y-90 Zevalin Dose | 0.4 mCi/kg (14.8 MBq/kg) | 0.3 mCi/kg (11.1 MBq/kg) | 0.4 mCi/kg (14.8 MBq/kg)
ANC
Median nadir (per mm^3) | 800 | 600 | 721
Per patient Incidence ANC <1000/mm^3 | 57% | 74% | 65%
Per Patient Incidence ANC <500/mm^3 | 30% | 35% | 26%
Median Duration (Days) [Day from last ANC ≥1000/mm^3 to first ANC ≥1000/mm^3 following nadir, censored at next treatment or death] ANC <1000/mm^3 | 22 | 29 | 29
Median Time to Recovery [Day from nadir to first count at level of Grade 1 toxicity or baseline] | 12 | 13 | 15
Platelets
Median nadir (per mm^3) | 41,000 | 24,000 | 42,000
Per Patient Incidence Platelets <50,000/mm^3 | 61% | 78% | 61%
Per Patient Incidence Platelets <10,000/mm^3 | 10% | 14% | 4%
Median Duration (Days) [Day from last platelet count ≥50,000/mm^3 to day of first platelet count ≥50,000/mm^3 following nadir, censored at next treatment or death] Platelets <50,000/mm^3 | 24 | 35 | 26
Median Time to Recovery | 13 | 14 | 14

Cytopenias were more severe and more prolonged among eleven (5%) patients who received Zevalin after first-line fludarabine or a fludarabine-containing chemotherapy regimen as compared to patients receiving non-fludarabine-containing regimens. Among these eleven patients, the median platelet nadir was 13,000/mm^3 with a median duration of platelets below 50,000/mm^3 of 56 days and the median time for platelet recovery from nadir to Grade 1 toxicity or baseline was 35 days. The median ANC was 355/mm^3, with a median duration of ANC below 1,000/mm^3 of 37 days and the median time for ANC recovery from nadir to Grade 1 toxicity or baseline was 20 days.

The median time to cytopenia was similar across patients with relapsed/refractory NHL and those completing first-line chemotherapy, with median ANC nadir at 61-62 days, platelet nadir at 49-53 days, and hemoglobin nadir at 68-69 days after Y-90-Zevalin administration.

Information on hematopoietic growth factor use and platelet transfusions is based on 211 patients with relapsed/refractory NHL and 206 patients following first-line chemotherapy. Filgrastim was given to 13% of patients and erythropoietin to 8% with relapsed or refractory disease; 14% of patients receiving Zevalin following first-line chemotherapy received granulocyte-colony stimulating factors and 5% received erythopoiesis-stimulating agents. Platelet transfusions were given to approximately 22% of all Zevalin-treated patients. Red blood cell transfusions were given to 20% of patients with relapsed or refractory NHL and 2% of patients receiving Zevalin following first-line chemotherapy.

Infections

In relapsed or refractory NHL patients, infections occurred in 29% of 349 patients during the first 3 months after initiating the Zevalin therapeutic regimen and 3% developed serious infections (urinary tract infection, febrile neutropenia, sepsis, pneumonia, cellulitis, colitis, diarrhea, osteomyelitis, and upper respiratory tract infection). Life-threatening infections were reported in 2% (sepsis, empyema, pneumonia, febrile neutropenia, fever, and biliary stent-associated cholangitis). From 3 months to 4 years after Zevalin treatment, 6% of patients developed infections; 2% were serious (urinary tract infection, bacterial or viral pneumonia, febrile neutropenia, perihilar infiltrate, pericarditis, and intravenous drug-associated viral hepatitis) and 1% were life-threatening infections (bacterial pneumonia, respiratory disease, and sepsis).

When administered following first-line chemotherapy (Table 2), Grade 3-4 infections occurred in 8% of Zevalin treated patients and in 2% of controls and included neutropenic sepsis (1%), bronchitis, catheter sepsis, diverticulitis, herpes zoster, influenza, lower respiratory tract infection, sinusitis, and upper respiratory tract infection.

Leukemia and Myelodysplastic Syndrome

Among 746 patients with relapsed/refractory NHL, 19 (2.6%) patients developed MDS/AML with a median follow-up of 4.4 years. The overall incidence of MDS/AML among the 211 patients included in the clinical studies was 5.2% (11/211), with a median follow-up of 6.5 years and median time to development of MDS/AML of 2.9 years. The cumulative Kaplan-Meier estimated incidence of MDS/secondary leukemia in this patient population was 2.2% at 2 years and 5.9% at 5 years. The incidence of MDS/AML among the 535 patients in the expanded access programs was 1.5% (8/535) with a median follow-up of 4.4 years and median time to development of MDS/AML of 1.5 years. Multiple cytogenetic abnormalities were described, most commonly involving chromosomes 5 and/or 7. The risk of MDS/AML was not associated with the number of prior treatments (0-1 versus 2-10).

Among 204 patients receiving Y-90-Zevalin following first-line treatment, 7 (3%) patients developed MDS/AML between approximately 2 to 7 years after Zevalin administration [see Warnings and Precautions (5.4)].

6.2 Post-Marketing Experience

The following adverse reactions have been identified during post-approval use of the Zevalin therapeutic regimen in hematologic malignancies. Because these reactions are reported voluntarily from a population of uncertain size, it is not always possible to reliably estimate their frequency or establish a causal relationship to drug exposure. Decisions to include these reactions in labeling are typically based on one or more of the following factors: (1) seriousness of the reaction, (2) frequency of reporting, or (3) strength of causal connection to the Zevalin therapeutic regimen.

- Cutaneous and mucocutaneous reactions: erythema multiforme, Stevens-Johnson syndrome, toxic epidermal necrolysis, bullous dermatitis, and exfoliative dermatitis [see Boxed Warning and Warnings and Precautions (5.3)].
- Infusion site erythema and ulceration following extravasation [see Warnings and Precautions (5.5)].
- Radiation injury in tissues near areas of lymphomatous involvement within a month of Zevalin administration.

6.3 Immunogenicity

As with all therapeutic proteins, there is a potential for immunogenicity. The detection of antibody formation is highly dependent on the sensitivity and specificity of the assay. Additionally, the observed incidence of antibody (including neutralizing antibody) positivity in an assay may be influenced by several factors including assay methodology, sample handling, timing of sample collection, concomitant medications, and underlying disease. For these reasons, comparisons of the incidence of antibodies to the Zevalin therapeutic regimen in the studies described below with the incidence of antibodies in other studies or to other products may be misleading.
HAMA and HACA response data on 446 patients from 8 clinical studies conducted over a 10-year time period are available. Overall, 11/446 (2.5%) had evidence of either HAMA formation (N=8) or HACA formation (N=4). Six of these patients developed HAMA/HACA after treatment with Zevalin and 5 were HAMA/HACA positive at baseline. Of the 6 who were HAMA/HACA positive, only one was positive for both. Furthermore, in 6 of the 11 patients, the HAMA/HACA reverted to negative within 2 weeks to 3 months. No patients had increasing levels of HAMA/HACA at the end of the studies.
Only 6/446 patients (1.3%) had developed evidence of antibody formation after treatment with Zevalin, and of these, many either reverted to negative or decreased over time. This data demonstrates that HAMA/HACA develop infrequently, are typically transient, and do not increase with time.

7 DRUG INTERACTIONS

Patients receiving medications that interfere with platelet function or coagulation should have more frequent laboratory monitoring for thrombocytopenia. No formal drug interaction studies have been performed with Zevalin.

8 USE IN SPECIFIC POPULATIONS

8.1 Pregnancy

Risk Summary

Based on its radioactivity, Y-90 Zevalin may cause fetal harm when administered to a pregnant woman [see Clinical Pharmacology (12.1)] . Immunoglobulins are known to cross the placenta. There are no available data on Zevalin use in pregnant women to inform a drug-associated risk of major birth defects and miscarriage. Advise women of childbearing potential to use adequate contraception for a minimum of twelve months. Inform women who become pregnant while receiving Zevalin of the potential fetal risks.

The estimated background risk of major birth defects and miscarriage for the indicated populations are unknown. All pregnancies have a background risk of birth defect, loss, or other adverse outcomes. However, the background risk in the U.S. general population of major birth defects is 2-4% and of miscarriage is 15-20% of clinically recognized pregnancies.

8.2 Lactation

Risk Summary

There are no data on the presence of Zevalin or its metabolites in human milk, the effects of Zevalin on the breastfed child, or its effects on milk production. Because human IgG is excreted in human milk, it is expected that Zevalin would be present in human milk. Due to the potential for serious adverse reactions in a breastfeeding child from Zevalin, advise lactating women to avoid breastfeeding during treatment with the Zevalin therapeutic regimen and for 6 months after the last dose.

8.3 Females and Males of Reproductive Potential

Zevalin may cause fetal harm when administered to a pregnant woman [see Use in Specific Populations (8.1)] .

Pregnancy Testing

Conduct pregnancy testing in females of reproductive potential prior to treatment with Zevalin.

Contraception

Females

Based on its radioactivity, Y-90 Zevalin may cause fetal harm. Advise females of reproductive potential to use effective contraceptive methods during treatment and for 12 months after the last dose of the Zevalin therapeutic regimen [see Clinical Pharmacology (12.1)] .

Males

Based on its radioactivity, Y-90 Zevalin may cause fetal harm. Advise males with female partners of reproductive potential to use effective contraceptive methods during treatment and for 12 months after the final dose of the Zevalin therapeutic regimen [see Clinical Pharmacology (12.1)].

Infertility

Based on its radioactivity, there is a potential risk that the Zevalin therapeutic regimen could cause toxic effects on the male and female gonads [see Clinical Pharmacology (12.1) and Nonclinical Toxicology (13.1)] .

8.4 Pediatric Use

The safety and effectiveness of Zevalin have not been established in pediatric patients.

8.5 Geriatric Use

Of 349 patients with relapsed/refractory NHL treated with the Zevalin therapeutic regimen in clinical studies, 38% (132 patients) were age 65 years and over, while 12% (41 patients) were age 75 years and over.

Of 414 patients enrolled in the FIT study (Zevalin following first-line chemotherapy) 206 patients received Zevalin. Of these patients 14% (29 patients) were 65 years and over, while 2% (4 patients) were 75 years and older. No overall differences in safety or effectiveness were observed between these subjects and younger subjects, but greater sensitivity of some older individuals cannot be ruled out.

10 OVERDOSAGE

Severe cytopenias which may require stem cell support have occurred at doses higher than the recommended maximum total dose of 32 mCi (1184 MBq).

11 DESCRIPTION

Zevalin (ibritumomab tiuxetan) is the immunoconjugate resulting from a stable thiourea covalent bond between the monoclonal antibody ibritumomab and the linker-chelator tiuxetan [N-[2-bis(carboxymethyl) amino]-3-(p-isothiocyanatophenyl)-propyl]-[N-[2-bis(carboxymethyl)amino]-2- (methyl)-ethyl]glycine. This linker-chelator provides a high affinity, conformationally restricted chelation site for Yttrium-90. The approximate molecular weight of ibritumomab tiuxetan is 148 kD. The antibody moiety of Zevalin is ibritumomab, a murine IgG1 kappa monoclonal antibody directed against the CD20 antigen.

Ibritumomab tiuxetan is a clear, colorless, sterile, pyrogen-free, preservative-free solution that may contain translucent particles. Each single-use vial includes 3.2 mg of ibritumomab tiuxetan in 2 mL of 0.9% Sodium Chloride.

Physical/Radiochemical Characteristics of Y-90

Yttrium-90 decays by emission of beta particles, with a physical half-life of 64.1 hours (2.67 days). The product of radioactive decay is non-radioactive Zirconium-90. The range of beta particles in soft tissue (χ90) is 5 mm. Radiation emission data for Y-90 are summarized in Table 5.

Table 5. Principal Y-90 Radiation Emission Data
Radiation | Mean % per Disintegration | Mean Energy (keV)
Beta minus | 100 | 750-935

External Radiation

The exposure rate for 1 mCi (37 MBq) of Y-90 is 8.3 x 10^-3 C/kg/hr (32 R/hr) at the mouth of an open Y-90 vial.

To allow correction for physical decay of Y-90, the fractions that remain at selected intervals before and after the time of calibration are shown in Table 6.

Table 6. Physical Decay Chart: Y-90 Half-life 2.67 Days (64.1 Hours)
Calibration Time (Hrs.) | Fraction Remaining | Calibration Time (Hrs.) | Fraction Remaining
-36 | 1.48 | 0 | 1.00
-24 | 1.30 | 1 | 0.99
-12 | 1.14 | 2 | 0.98
-8 | 1.09 | 3 | 0.97
-7 | 1.08 | 4 | 0.96
-6 | 1.07 | 5 | 0.95
-5 | 1.06 | 6 | 0.94
-4 | 1.04 | 7 | 0.93
-3 | 1.03 | 8 | 0.92
-2 | 1.02 | 12 | 0.88
-1 | 1.01 | 24 | 0.77
0 | 1.00 | 36 | 0.68

12 CLINICAL PHARMACOLOGY

12.1 Mechanism of Action

Ibritumomab tiuxetan binds specifically to the CD20 antigen (human B-lymphocyte-restricted differentiation antigen, Bp35). The apparent affinity (KD) of ibritumomab tiuxetan for the CD20 antigen ranges between approximately 14 to 18 nM. The CD20 antigen is expressed on pre-B and mature B lymphocytes and on > 90% of B-cell non-Hodgkin’s lymphomas (NHL). The CD20 antigen is not shed from the cell surface and does not internalize upon antibody binding.

The chelate tiuxetan, which tightly binds Y-90, is covalently linked to ibritumomab. The beta emission from Y-90 induces cellular damage by the formation of free radicals in the target and neighboring cells.

Ibritumomab tiuxetan binding was observed in vitro on lymphoid cells of the bone marrow, lymph node, thymus, red and white pulp of the spleen, and lymphoid follicles of the tonsil, as well as lymphoid nodules of other organs such as the large and small intestines.

12.2 Pharmacodynamics

In clinical studies, administration of the Zevalin therapeutic regimen resulted in sustained depletion of circulating B cells. At four weeks, the median number of circulating B cells was zero (range, 0-1084/mm^3). B-cell recovery began at approximately 12 weeks following treatment, and the median level of B cells was within the normal range (32 to 341/mm^3) by 9 months after treatment. Median serum levels of IgG and IgA remained within the normal range throughout the period of B-cell depletion. Median IgM serum levels dropped below normal (median 49 mg/dL, range 13-3990 mg/dL) after treatment and recovered to normal values by 6-months post therapy.

12.3 Pharmacokinetics

Pharmacokinetic and biodistribution studies were performed using In-111 Zevalin (5 mCi [185 MBq] In-111, 1.6 mg ibritumomab tiuxetan). In an early study designed to assess the need for pre-administration of unlabeled antibody, only 18% of known sites of disease were imaged when In-111 Zevalin was administered without unlabeled ibritumomab. When preceded by unlabeled ibritumomab (1.0 mg/kg or 2.5 mg/kg), In-111 Zevalin detected 56% and 92% of known disease sites, respectively. These studies were conducted with a Zevalin therapeutic regimen that included unlabeled ibritumomab.

In pharmacokinetic studies of patients receiving the Zevalin therapeutic regimen, the mean effective half-life for Y-90 activity in blood was 30 hours, and the mean area under the fraction of injected activity (FIA) vs. time curve in blood was 39 hours. Over 7 days, a median of 7.2% of the injected activity was excreted in urine.

13 NONCLINICAL TOXICOLOGY

13.1 Carcinogenesis, Mutagenesis, Impairment of Fertility

Carcinogenicity and mutogenicity studies have not been conducted. However, radiation is a potential carcinogen and mutagen.

No animal studies have been performed to determine the effects of Zevalin on fertility in males or females. In clinical studies, the Zevalin therapeutic regimen results in a significant radiation dose to the testes: the radiation dose to the ovaries has not been established [see Dosage and Administration (2.5)]. There is a potential risk that the Zevalin therapeutic regimen could cause toxic effects on the male and female gonads. Effective contraceptive methods should be used during treatment and for up to 12 months following the Zevalin therapeutic regimen.

13.2 Animal Toxicology and/or Pharmacology

Animal reproductive toxicology studies of the Zevalin therapeutic regimen have not been conducted. Because the Zevalin therapeutic regimen includes the use of rituximab, also see prescribing information for rituximab.

14 CLINICAL STUDIES

14.1 Relapsed or Refractory, Low-grade or Follicular Lymphoma

A study to evaluate the efficacy and safety of Zevalin (referred to as Study 106-06) was a single arm study of 54 patients with relapsed follicular lymphoma, who were refractory to rituximab treatment. Patients had a World Health Organization (WHO) Performance Status (PS) 0-2, <25% bone marrow involvement by NHL, no prior bone marrow transplantation, and acceptable hematologic, renal, and hepatic function. Refractoriness to rituximab was defined as failure to achieve a complete or partial response or time-to-disease-progression (TTP) of < 6 months. The main efficacy outcome measure of the study was the overall response rate (ORR) using the International Workshop Response Criteria (IWRC). Other efficacy outcome measures included time-to-disease-progression (TTP) and duration of response (DR). Table 7 summarizes efficacy data from Study 106-06.

Another study to evaluate the efficacy and safety of Zevalin (referred to as Study 106-04) was a randomized (1:1), open-label, multicenter study comparing the Zevalin therapeutic regimen with rituximab. The trial was conducted in 130 patients with relapsed or refractory low-grade or follicular non-Hodgkin's lymphoma (NHL); no patient had received prior rituximab. Patients had histologically confirmed NHL requiring therapy, a WHO PS 0-2, <25% bone marrow involvement by NHL, no prior bone marrow transplantation, and acceptable hematologic function. Sixty-four patients received the Zevalin therapeutic regimen, and 66 patients received rituximab given as an IV infusion at 375 mg per m^2 weekly times 4 doses. The main efficacy outcome measure of the study was ORR using the IWRC. The ORR was significantly higher for patients receiving the Zevalin therapeutic regimen (83% vs. 55%, p<0.001). Time-to-disease-progression was not significantly different between study arms. Table 7 summarizes efficacy data from Study 106-04.

Table 7 . Summary of Efficacy Data [IWRC: International Workshop Response Criteria]
 | Study 106-06 | Study 106-04
 | Zevalin Therapeutic regimen N = 54 | Zevalin Therapeutic regimen N = 64 | Rituximab N = 66
Overall Response Rate (%) | 74 | 83 | 55
Complete Response Rate [CRu and CR: Unconfirmed and confirm complete response] (%) | 15 | 38 | 18
Median DR [Estimated with observed range] [Duration of response: interval from the onset of response to disease progression] (Months) [Range [“+” indicates an ongoing response] ] | 6.4 [0.5-49.9+] | 14.3 [1.8-47.6+] | 11.5 [1.2-49.7+]
Median TTP [Time to Disease Progression: interval from the first infusion to disease progression] (Months) [Range] | 6.8 [1.1-50.9+] | 12.1 [2.1-49.0+] | 10.1 [0.7-51.3+]

A single-arm study to evaluate the efficacy and safety of Zevalin (referred to as Study 106-05) was conducted in 30 patients, of whom 27 had relapsed or refractory low-grade, follicular NHL and a platelet count 100,000 to 149,000/mm^3. Patients with ≥ 25% lymphomatous marrow involvement, prior myeloablative therapy with stem cell support, prior external beam radiation to > 25% of active marrow or neutrophil count <1,500/mm^3 were ineligible for Study 106-05. All patients received Y-90 Zevalin [0.3 mCi per kg (11.1 MBq per kg)]. Objective, durable clinical responses were observed [89% ORR (95% CI: 70-97%) with a median duration of response of 11.6 months (range: 1.0-42.4+ months)].

14.2 Follicular, B-Cell NHL Upon Completion of First-Line Chemotherapy

The FIT (First-line Indolent Trial) study (NCT00185393) was a multi-center, randomized, open-label study conducted in patients with follicular NHL with a partial (PR) or complete response (CR/CRu) upon completion of first-line chemotherapy. Randomization was stratified by center and response to first-line therapy (CR or PR). Key eligibility criteria were <25% bone marrow involvement, no prior external beam radiation or myeloablative therapy, and recovery of platelets to normal levels. Patients were randomized to receive Zevalin (n=208) or no further therapy (n=206). Y-90 Zevalin was administered at least 6 weeks but no more than 12 weeks following the last dose of chemotherapy. The main efficacy outcome measure was progression-free survival (PFS) assessed by study investigators using the International Workshop to Standardize Response Criteria for non-Hodgkin’s Lymphoma (1999).

Among the 414 patients, 49% were male, 99% were Caucasian, 12% were ≥65 years old, 83% had a WHO performance status of 0, and 65% had Stage IV disease. Thirty-nine (9.5%) patients received single agent chlorambucil, 22 (5%) patients received fludarabine or a fludarabine-containing regimen, 294 (71%) patients received cyclophosphamide-containing combination chemotherapy [CHOP (31%); CHOP-like (15%); CVP/COP (26%)] and 59 (14%) patients received rituximab-containing combination chemotherapy as first-line treatment.

Progression-free survival was significantly prolonged among Zevalin-treated patients compared to those receiving no further treatment [median PFS 38 months vs. 18 months; HR 0.46 (95% CI: 0.35, 0.60) p<0.0001 Cox model stratified by response to first-line therapy and initial treatment strategy (immediate vs. watch-and-wait)]. The number of patients who died was too small to permit a reliable comparison on survival.

The results for PFS are presented in Figure 1.

16 HOW SUPPLIED/STORAGE AND HANDLING

A kit is used for preparing Y-90 radiolabeled Zevalin (NDC 72893-007-04). The contents of all vials are sterile, pyrogen-free, contain no preservatives, and are not radioactive. The kit contains four identification labels and the following four vials:

1. One (1) Zevalin vial containing 3.2 mg ibritumomab tiuxetan in 2 mL 0.9% Sodium Chloride as a clear, colorless solution.
2. One (1) 50 mM Sodium Acetate Vial containing 13.6 mg Sodium Acetate trihydrate in 2 mL Water for Injection, USP as a clear, colorless solution.
3. One (1) Formulation Buffer Vial containing 750 mg Albumin (Human), 76 mg Sodium Chloride, 28 mg Sodium Phosphate Dibasic Dodecahydrate, 4 mg Pentetic Acid, 2 mg Potassium Phosphate Monobasic and 2 mg Potassium Chloride in 10 mL Water for Injection, pH 7.1 as a clear yellow to amber colored solution.
4. One (1) empty Reaction Vial.

Yttrium-90 Chloride Sterile Solution is shipped directly from the supplier upon placement of an order for the Y-90 Zevalin kit.

Rituximab must be ordered separately.

Storage

Store the kit at 2-8°C (36-46°F). Do not freeze.

17 PATIENT COUNSELING INFORMATION

Advise patients:

- To contact a healthcare professional for severe signs and symptoms of infusion reactions.
- To take premedications as prescribed [see Dosage and Administration (2.2) and Warnings and Precautions (5.1)].
- To report any signs or symptoms of cytopenias (bleeding, easy bruising, petechiae or purpura, pallor, weakness or fatigue) [see Warnings and Precautions (5.2)].
- To avoid medications that interfere with platelet function, except as directed by a healthcare professional [see Warnings and Precautions (5.2)].
- To seek prompt medical evaluation for diffuse rash, bullae, or desquamation of the skin or oral mucosa [see Warnings and Precautions (5.3)].
- To immediately report symptoms of infection (e.g. pyrexia) [see Adverse Reactions (6.2)].
- That immunization with live viral vaccines is not recommended for 12 months following the Zevalin therapeutic regimen [see Warnings and Precautions (5.6)].
- To use effective contraceptive methods during treatment and for a minimum of 12 months following Zevalin therapy [see Warnings and Precautions (5.8)], Use in Specific Populations (8.1, 8.3) and Nonclinical Toxicology (13.1)].
- To discontinue breastfeeding during and for 6 months after the last dose of Zevalin treatment [see Use In Specific Populations (8.2)].

Zevalin ® (ibritumomab tiuxetan)

Manufactured by:
Acrotech Biopharma Inc.
East Windsor, NJ 08520
U.S. License No.2159

Zevalin ® is a registered trademark of Acrotech Biopharma Inc and its subsidiaries.

Protected by U.S. Patent Nos. 5,736,137, 5,776,456, 5,843,439, 6,207,858, 6,399,061, 6,682,734, 6,994,840, 7,229,620, 7,381,560, 7,422,739 and other patents and patents pending.